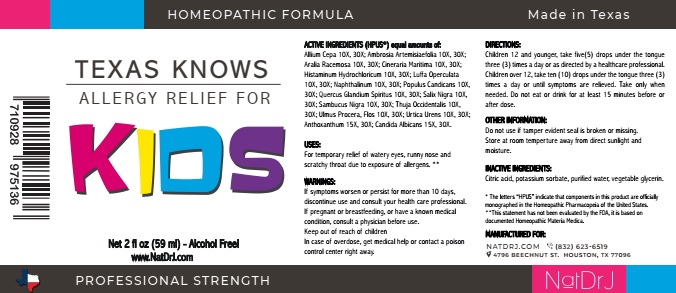 DRUG LABEL: Texas Knows Allergy Relief For Kids
NDC: 71559-202 | Form: LIQUID
Manufacturer: NaturoDRJ Enterprises
Category: homeopathic | Type: HUMAN OTC DRUG LABEL
Date: 20190103

ACTIVE INGREDIENTS: ONION 10 [hp_X]/59 mL; AMBROSIA ARTEMISIIFOLIA 10 [hp_X]/59 mL; ARALIA RACEMOSA ROOT 10 [hp_X]/59 mL; JACOBAEA MARITIMA 10 [hp_X]/59 mL; HISTAMINE DIHYDROCHLORIDE 10 [hp_X]/59 mL; LUFFA OPERCULATA FRUIT 10 [hp_X]/59 mL; NAPHTHALENE 10 [hp_X]/59 mL; POPULUS BALSAMIFERA LEAF BUD 10 [hp_X]/59 mL; QUERCUS ROBUR NUT 10 [hp_X]/59 mL; SALIX NIGRA BARK 10 [hp_X]/59 mL; SAMBUCUS NIGRA FLOWERING TOP 10 [hp_X]/59 mL; THUJA OCCIDENTALIS LEAFY TWIG 10 [hp_X]/59 mL; ULMUS PROCERA FLOWERING TWIG 10 [hp_X]/59 mL; URTICA URENS 10 [hp_X]/59 mL; ANTHOXANTHUM ODORATUM 15 [hp_X]/59 mL; CANDIDA ALBICANS 15 [hp_X]/59 mL
INACTIVE INGREDIENTS: WATER; GLYCERIN; CITRIC ACID MONOHYDRATE; POTASSIUM SORBATE

TEXAS KNOWS ALLERGY RELIEF FOR KIDS

ACTIVE INGREDIENT

ACTIVE INGREDIENTS (HPUS*) - equal amounts of: Allium Cepa 10X, 30X; Ambrosia Artemisiaefolia 10X, 30X; Aralia Racemosa 10X, 30X; Cineraria Maritima 10X, 30X; Histaminum Hydrochloricum 10X, 30X; Luffa Operculata 10X, 30X; Naphthalinum 10X, 30X; Populus Candicans 10X, 30X; Quercus Glandium Spiritus 10X, 30X; Salix Nigra 10X, 30X; Sambucus Nigra 10X, 30X; Thuja Occidentalis 10X, 30X; Ulmus Procera, Flos 10X, 30X; Urtica Urens 10X, 30X; Anthoxanthum 15X, 30X; Candida Albicans 15X, 30X.

*The letters ''HPUS'' indicate that components in this product ard officially monographed in the Homeopathic Pharmacopeia of the United States.

** This statement has not been evaluated by the FDA, it is based on documented Homeopathic Materia Medica.

INDICATIONS AND USAGE

USES: For temporary relief of watery eyes, runny nose and scratchy throat due to exposure of allergens.**

Warnings:

If symptoms worsen or persist for more than 10 days, discontinue use and consult your health care professional.

If pregnant or breastfeeding, or have a known medical condition, consult a physician before use.

Keep out of reach of children.

In case of overdose, get medical help or contact a poison control center right away.

Keep out of reach of children.

DIRECTIONS:

Children 12 and younger, take five (5) drops under the tongue three (3) times a day or as directed by a healthcare professional. Children over 12, take ten (10) drops under the tongue three (3) times a day or until symptoms are relieved. Take only when needed. Do not eat or drink for at least 15 minutes before or after dose.

OTHER INFORMATION:

Do not use if tamper evident seal is broken or missing.

Store at room temperature away from direct sunlight and moisture.

INACTIVE INGREDIENTS:

Citric acid, potassium sorbate, purified water, vegetable glycerin.

QUESTIONS

MANUFACTURED FOR:

NATDRJ.COM (832) 623-6519

HOUSTON, TX 77096

4796 BEECHNUT ST. HOUSTON, TX 77096

PACKAGE LABEL

HOMEOPATHIC FORMULA Made in Texas

TEXAS KNOWS

ALLERGY RELIEF FOR

KIDS

Net 2 fl oz (59 ml) - Alcohol Free!

www.NatDrJ.com

PROFESSIONAL STRENGTH

PURPOSE

USES: For temporary relief of watery eyes, runny nose and scratchy throat due to exposure of allergens.**